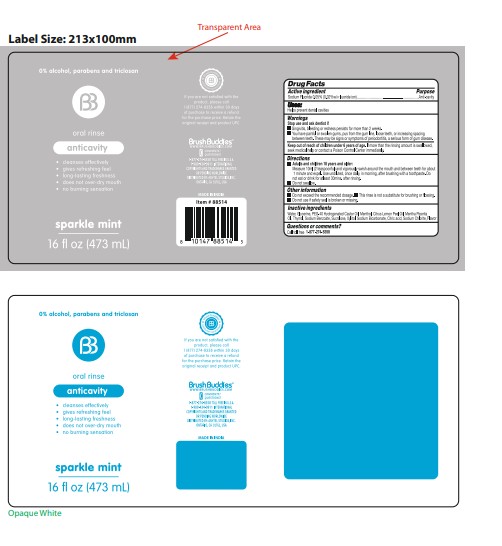 DRUG LABEL: Brush Buddies Oral Rinse Sparkle Mint
NDC: 70108-206 | Form: MOUTHWASH
Manufacturer: ASHTEL STUDIOS, INC
Category: otc | Type: HUMAN OTC DRUG LABEL
Date: 20250715

ACTIVE INGREDIENTS: SODIUM FLUORIDE 0.2 mg/1 mL
INACTIVE INGREDIENTS: WATER; GLYCERIN; POLYOXYL 40 HYDROGENATED CASTOR OIL; MENTHOL, UNSPECIFIED FORM; PEPPERMINT OIL; THYMOL; LEMON OIL, COLD PRESSED; SODIUM BENZOATE; SUCRALOSE; XYLITOL; SODIUM BICARBONATE; CITRIC ACID MONOHYDRATE; SODIUM CHLORITE

Brush Buddies Oral Rinse, Sparkle Mint

Active ingredient

Sodium Fluoride 0.05% (0.02%w/v fluoride ion)

Purpose

Anti-cavity

Uses:

Helps prevent dental cavities

Warnings

Stop use and ask dentist if

- Gingivitis, bleeding or redness persists for more than 2 weeks.
- You have painful or swollen gums, pus from the gum line, loose teeth, or increasing spacing between teeth. These may be signs or symptoms of periodontitis, a serious form of gum disease.

Keep out of reach of children under 6 years of age.

If more than the rinsing amount is swallowed, seek medical help or contact a Poison Control Center immediately.

Directions

- Adults and children 18 years and older:Measure 10ml (2 teaspoonful) and vigorously swish around the mouth and between teeth for about 1 minute and expel. Use undiluted, once daily, in morning, after brushing with a toothpaste. Do not eat or drink for atleast 30min. after rinsing.
- Do not swallow.

Other information

- Do not exceed the recommended dosage.
- This rinse is not a substitute for brushing or flossing.
- Do not use if safety seal is broken or missing.

Inactive ingredients

Water, Glycerine, PEG-40 Hydrogenated Castor Oil, Menthol, Citrus Lemon Peel Oil, Mentha Piperita Oil, Thymol, Sodium Benzoate, Sucralose, Xylitol, Sodium Bicarbonate, Citric acid, Sodium Chlorite, Flavour

Questions or comments?

Call toll free 1-877-274-8358